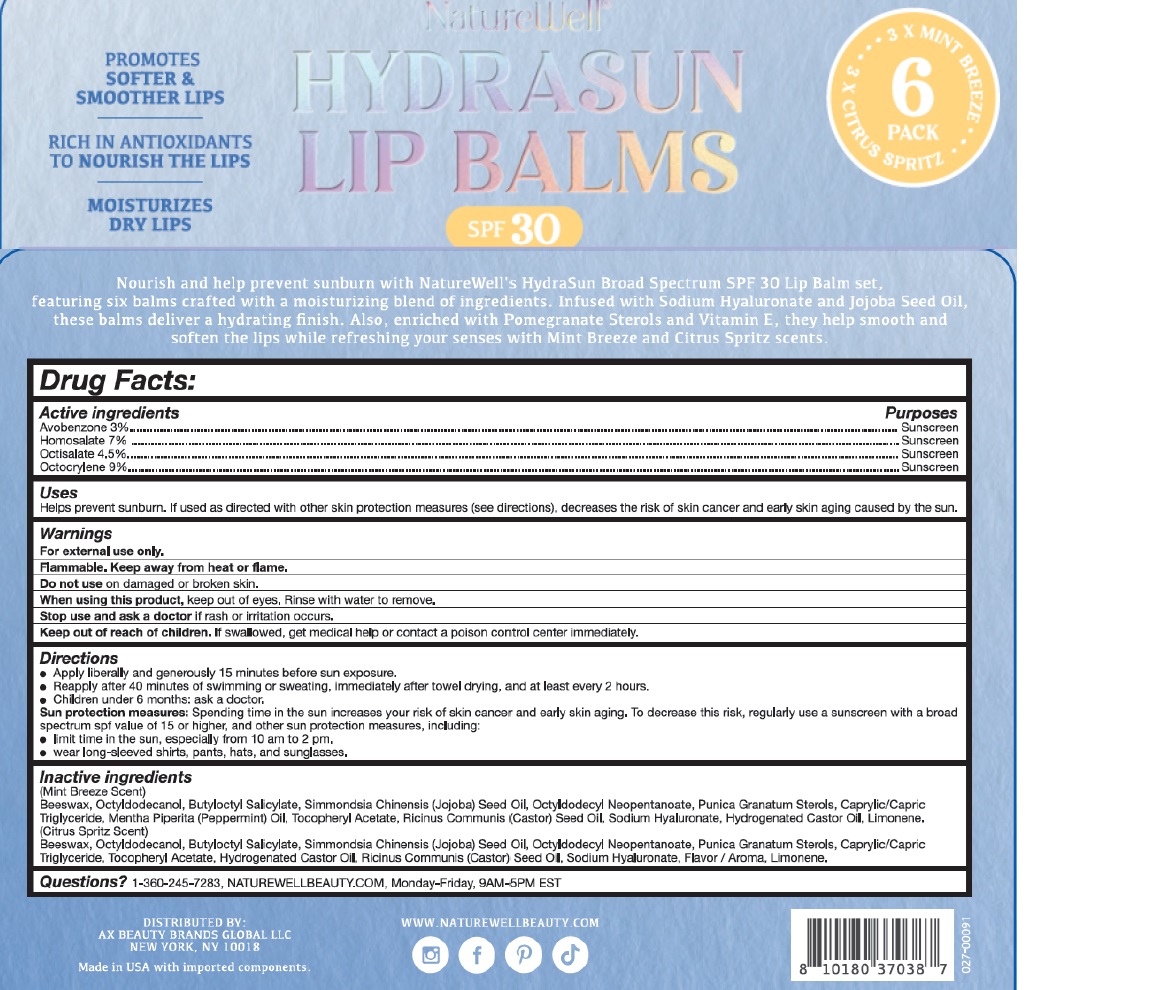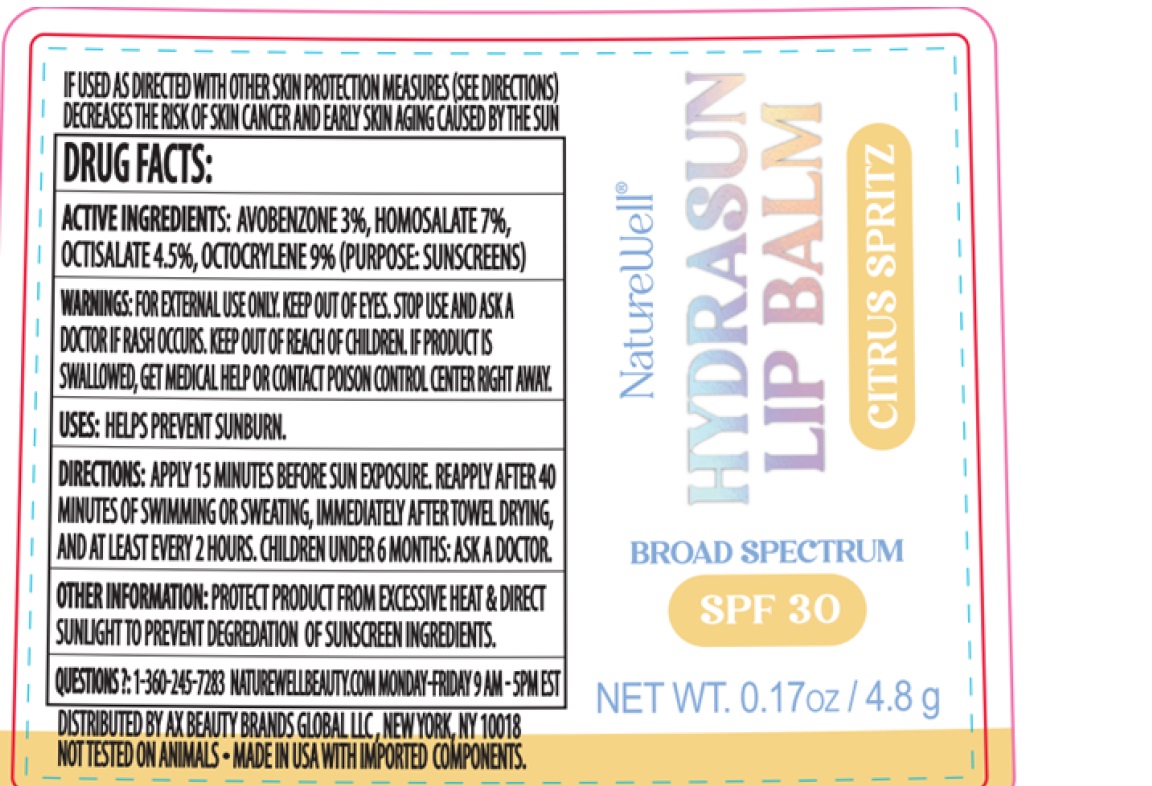 DRUG LABEL: NATUREWELL HYDRASUN LIP BALM SPF30 CITRUS SPRITZ
NDC: 10637-3200 | Form: LIPSTICK
Manufacturer: Port Jervis Laboratories, Inc.
Category: otc | Type: HUMAN OTC DRUG LABEL
Date: 20250526

ACTIVE INGREDIENTS: OCTISALATE 4.5 g/100 g; HOMOSALATE 7 g/100 g; AVOBENZONE 3 g/100 g; OCTOCRYLENE 9 g/100 g
INACTIVE INGREDIENTS: BUTYLOCTYL SALICYLATE; RICINUS COMMUNIS (CASTOR) SEED OIL; OCTYLDODECANOL; SIMMONDSIA CHINENSIS (JOJOBA) SEED OIL; OCTYLDODECYL NEOPENTANOATE; SODIUM HYALURONATE; CAPRYLIC/CAPRIC TRIGLYCERIDE; PUNICA GRANATUM STEROLS; HYDROGENATED CASTOR OIL; BEESWAX; .ALPHA.-TOCOPHEROL ACETATE

NATUREWELL HYDRASUN LIP BALM SPF30 CITRUS SPRITZ

PURPOSE

SUNSCREEN

USES

HELPS PREVENT SUNBURN. IF USED AS DIRECTED WITH OTHER SUN PROTECTION MEASURES (SEE DIRECTIONS), DECREASES THE RISK OF SKIN CANCER AND EARLY SKIN AGING CAUSED BY THE SUN.

ACTIVE INGREDIENT

AVOBENZONE 3.0%

HOMOSALATE 7.0%

OCTISALATE 4.5%

OCTOCRYLENE 9.0%

WARNINGS

For external use only.

Flammable. Keep away from heat or flame.

Do not use on damaged or broken skin.

When using this product, keep out of eyes. Rinse with water to remove.

Stop use and ask a doctor if rash or irritation occurs.

Keep out of reach of children.If swallowed, get medical help or contact a Poison Control Center immediately.

DIRECTIONS

- Apply liberally and generously 15 minutes before sun exposure.
- Reapply after 40 minutes of swimming or sweating, immediately after towel drying, and at least every 2 hours.
- Children under 6 months: ask a doctor.

Sun Protection Measures.Spending time in the sun increases your risk of skin cancer and early skin aging. To decrease this risk, regularly use a sunscreen with a Broad Spectrum SPF 15 value or higher along with other sun protection measures including:

- limit time in the sun, especially from 10 a.m. – 2 p.m.
- wear long-sleeved shirts, pants, hats and sunglasses.

OTHER INFORMATION

- Protect this product from excessive heat and direct sun to prevent degredation of sunscreen ingredients.

INACTIVE INGREDIENTS

BEESWAX, OCTYLDODECANOL, BUTYLOCTYL SALICYLATE, SIMMONDSIA CHINENSIS (JOJOBA) SEED OIL, OCTYLDODECYL NEOPENTANOATE, CAPRYLIC/CAPRIC TRIGLYCERIDE, PUNICA GRANATUM STEROLS, TOCOPHERYL ACETATE, FLAVOR (AROMA), RICINUS COMMUNIS (CASTOR) SEED OIL, SODIUM HYALURONATE, HYDROGENATED CASTOR OIL

QUESTIONS?

1- 360-245-7283, NATUREWELLBEAUTY.COM, Monday – Friday, 9 AM – 5 PM EST